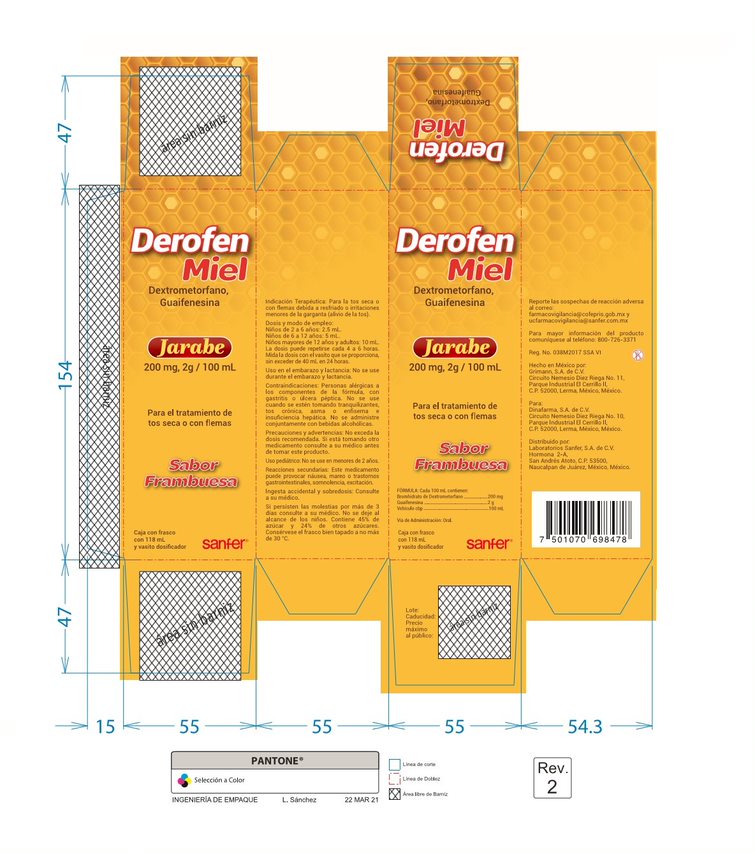 DRUG LABEL: DEROFEN MIEL
NDC: 81660-435 | Form: SYRUP
Manufacturer: Grimann, S.A. de C.V.
Category: otc | Type: HUMAN OTC DRUG LABEL
Date: 20210406

ACTIVE INGREDIENTS: PROPYLENE GLYCOL 11.8 g/1 U
INACTIVE INGREDIENTS: GLYCERIN 5.9 g/1 U; HONEY 28.32 g/1 U; METHYLPARABEN 0.1 g/1 U; SUCROSE 53.1 g/1 U; PROPYLPARABEN 0.177 g/1 U; DEUDEXTROMETHORPHAN HYDROBROMIDE 0.236 g/1 U; ALCOHOL 0.481 mL/1 U; WATER 118 mL/1 U; ACESULFAME POTASSIUM 0.354 g/1 U; GUAIFENESIN .BETA.-ISOMER 2.36 g/1 U

DEROFEN MIEL.

DROG DOSAGE INSTRUCTIONS FOR ADMINISTRATION:
Adults and children 12 years and over: 1 tablet a day.

WARNINGS AND PRECAUTIONS: Do not exceed the recommended
dosage. If you are taking other medicines, consult your doctor.
Do not use loratadine with alcohol or other central nervous
system depressants. Children under 12 years old: do not use
PEDIATRIC USE: Children under 12 years of age: do not use.
PREGNANCY AND BREASTFEEDING: Do not use during pregnancy
or breastfeeding.
CONTRAINDICATIONS: Do not use in case of hypersensitivity to
the ingredients.
ADVERSE REACTIONS: Fatigue, headache, dry mouth, nausea,
gastritis, skin rash.
ACCIDENTAL INGESTION AND OVERDOSE: Reported symptoms in
case of overdose: sleepiness, tachycardia, headache.
The treatment that should be started immediately is symptomatic
and adjuvant. Keep out of reach of children. If symptoms persist
for more than 5 days, consult your doctor.
Do not store above 86°F. Keep this container tightly closed.

TRANSLATION And Correction

Boxed Warning
• Indications and Usage
• Dosage and Administration
• Contraindications
• Warnings and Precautions

INACTIVE INGREDIENTES: Magnesium Stearate, Lactose
Starch Corn,Water

Therapeutic indications: Indicated for the symptomatic
treatment of manifestations related to allergic rhinitis
such as:
sneezing, runny nose and watery eyes.
Also indicated for chronic hives and other manifestations
of allergic dermatological disorder

Keep out of reach of children. In case of overdose, get
medical help or contact a Poison Control Center right
away.

WARNINGS AND PRECAUTIONS: Do not exceed the recommended
dosage. If you are taking other medicines, consult your doctor.
Do not use loratadine with alcohol or other central nervous
system depressants. Children under 12 years old: do not use
PEDIATRIC USE: Children under 12 years of age: do not use.
PREGNANCY AND BREASTFEEDING: Do not use during pregnancy
or breastfeeding.
CONTRAINDICATIONS: Do not use in case of hypersensitivity to
the ingredients.
ADVERSE REACTIONS: Fatigue, headache, dry mouth, nausea,
gastritis, skin rash.
ACCIDENTAL INGESTION AND OVERDOSE: Reported symptoms in
case of overdose: sleepiness, tachycardia, headache.
The treatment that should be started immediately is symptomatic
and adjuvant. Keep out of reach of children. If symptoms persist
for more than 5 days, consult your doctor.
Do not store above 86°F. Keep this container tightly closed.

PURPOSE

PURPOUSE/ USES
Indicated for the symptomatic treatment of
manifestations related to allergic rhinitis such as:
▪ runny nose
▪ sneezing
▪ itchy, watery eyes
▪ itching of the nose or throat